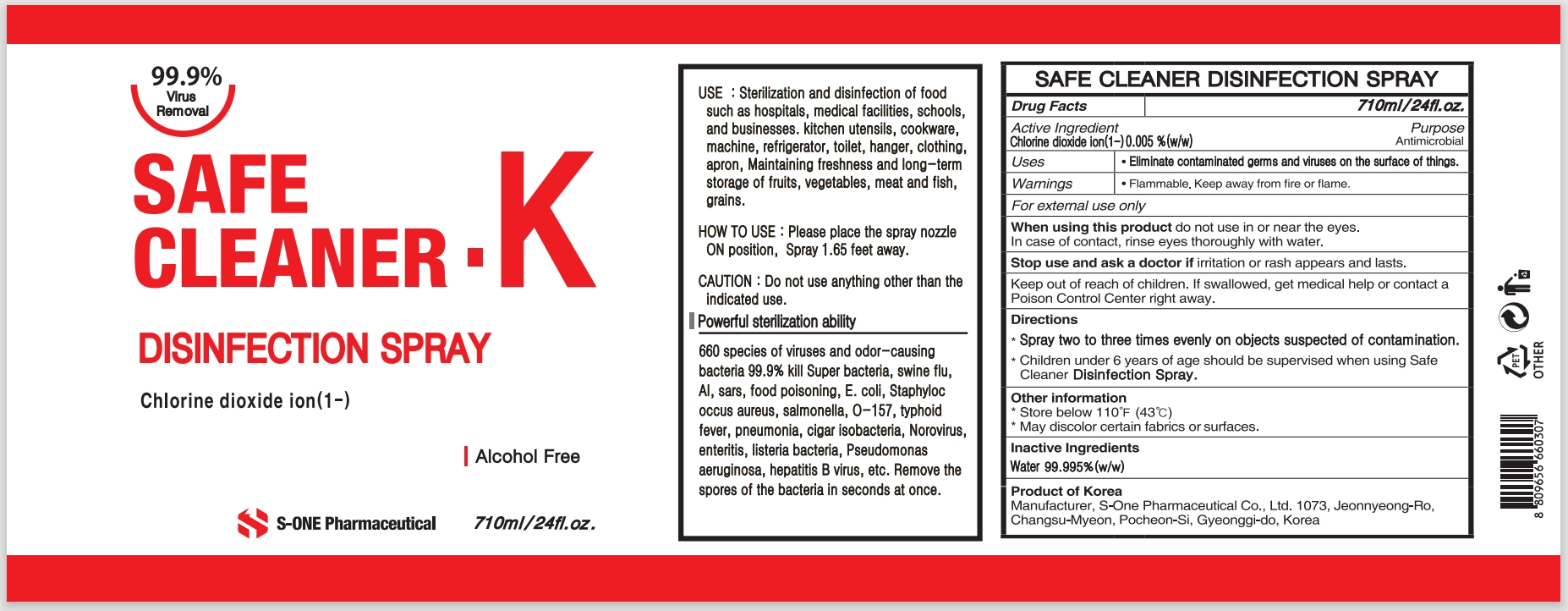 DRUG LABEL: SAFE CLEANER K
NDC: 74721-0050 | Form: LIQUID
Manufacturer: S-ONE PHARMACEUTICAL INC
Category: otc | Type: HUMAN OTC DRUG LABEL
Date: 20201126

ACTIVE INGREDIENTS: CHLORITE ION 0.005 mg/100 mL
INACTIVE INGREDIENTS: WATER

74721-0050

Active Ingredient

Chlorine dioxide ion(1-) 0.005%

Purpose

Antimicrobial

Uses

Eliminate contaminated germs and viruses on the surface of things.

Warnings

Flammable. Keep away from fire or flame.

For external use only

When using this product

do not use in or near the eyes.

In case of contact, rinse eyes thoroughly with water.

Stop use and ask a doctor if

irritation or rash appears and lasts.

Keep out of reach of children. If swallowed, get medical help or contact a Poison Control Center right away.

Directions

Spray two to three times evenly on objects suspected of contamination.

Children under 6 years of age should be supervised when using Safe Cleaner Disinfection Spray.

Other information

Store Below 110℉ (43℃)

May discolor certain fabrics or surfaces.

Inactive Water

Water 99.995%(w/w)